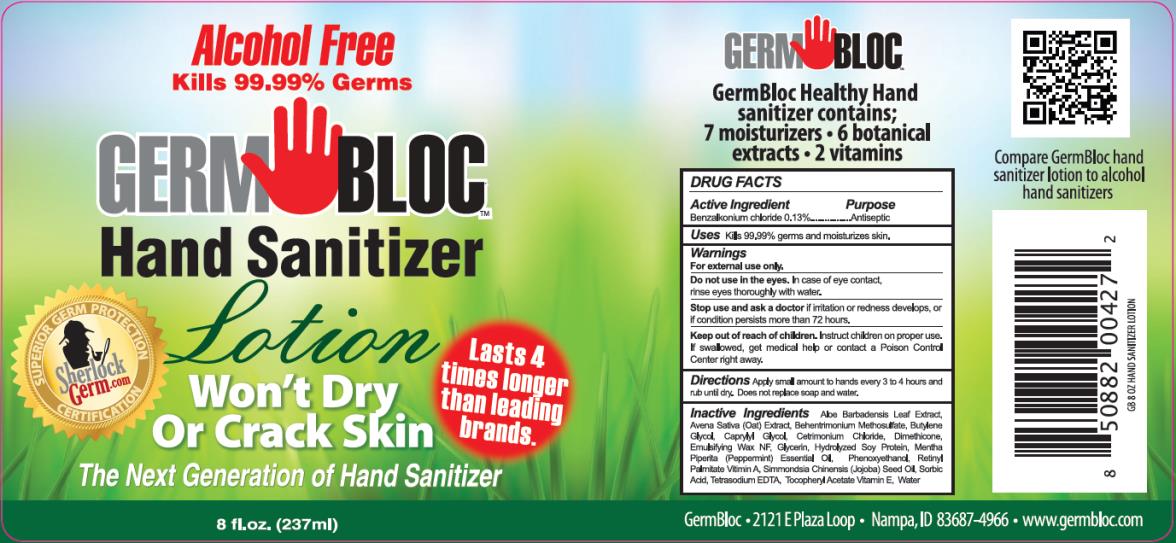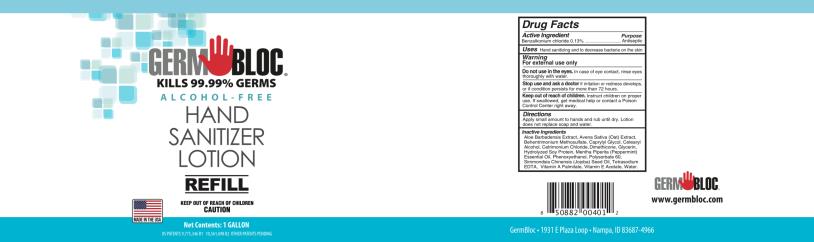 DRUG LABEL: Germ Bloc Hand Sanitizer
NDC: 69243-0610 | Form: LOTION
Manufacturer: Willspeed Technologies LLC
Category: otc | Type: HUMAN OTC DRUG LABEL
Date: 20220114

ACTIVE INGREDIENTS: BENZALKONIUM CHLORIDE 0.0013 g/1 mL
INACTIVE INGREDIENTS: ALOE VERA LEAF; AVENA SATIVA LEAF; BEHENTRIMONIUM METHOSULFATE; BUTYLENE GLYCOL; CAPRYLYL GLYCOL; CETRIMONIUM CHLORIDE; DIMETHICONE; GLYCERIN; SOY PROTEIN; PEPPERMINT OIL; PHENOXYETHANOL; VITAMIN A PALMITATE; JOJOBA OIL; SORBIC ACID; EDETATE SODIUM; ALPHA-TOCOPHEROL ACETATE; WATER

Germ Bloc Hand Sanitizer Lotion

DRUG FACTS

Active Ingredient

Benzalkonium chloride 0.13%

Purpose

Antiseptic

Uses

Kills 99.99 % germs and moisturizes skin.

Warnings

For external use only.

Do not use in the eyes.

In case of eye contact, rinse eyes thoroughly with water.

Stop use and ask a doctor

if irritation or redness develops, or if condition persists more than 72 hours.

Keep out of reach of children.

Instruct children on proper use. If swallowed, get medical help or contact a Poison Control Center right away.

Directions

Apply a small amount to hands every 3 to 4 hours and rub until dry. Does not replace soap and water.

Inactive Ingredients

Aloe Barbadensis Leaf Extract, Avena Sativa (Oat) Extract, Behentrimonium Methosulfate, Butylene Glycol, Caprylyl Glycol, Centrimonium Chloride, Dimethicone, Emulsifying Wax NF, Glycerin, Hydrolyzed Soy Protein, Mentha Piperita (Peppermint) Essential Oil, Phenoxyethanol, Retinyl Palmitate Vitamin A, Simmondsia Chinensis (Jojoba) Seed Oil, Sorbic Acid, Tetrasodium EDTA, Tocopheryl Acetate Vitamin E, Water

DRUG FACTS

Active Ingredient

Benzalkonium chloride 0.13%

Purpose

Antiseptic

Uses

Kills 99.99 % germs and moisturizes skin.

Warnings

For external use only.

Do not use in the eyes.

In case of eye contact, rinse eyes thoroughly with water.

Stop use and ask a doctor

if irritation or redness develops, or if condition persists more than 72 hours.

Keep out of reach of children.

Instruct children on proper use. If swallowed, get medical help or contact a Poison Control Center right away.

Directions

Apply a small amount to hands every 3 to 4 hours and rub until dry. Does not replace soap and water.

Inactive Ingredients

Aloe Barbadensis Extract, Avena Sativa (Oat) Extract, Behentrimonium Methosulfate, Caprylyl Glycol, Cetearyl Alcohol, Cetrimonium Chloride, Dimethicone, Glycerin, Hydrolyzed Soy Protein, Mentha Piperita (Peppermint) Essential Oil, Phenoxyethanol, Polysorbate 60, Simmondsia Chinensis (Jojoba) Seed Oil, Tetrasodium EDTA, Vitamin A Palmitate, Vitamin E Acetate, Water.

PRINCIPAL DISPLAY PANEL

ALCOHOL-FREE
Kills 99.99% of Germs
GERM BLOCTM
Hand Sanitizer
Lotion
8 fl. oz. (237 ml)

PRINCIPAL DISPLAY PANEL

GERM BLOC®
KILLS 99.99% GERMS
ALCOHOL-FREE
HAND SANITIZER
LOTION
Net Contents: 1 GALLON